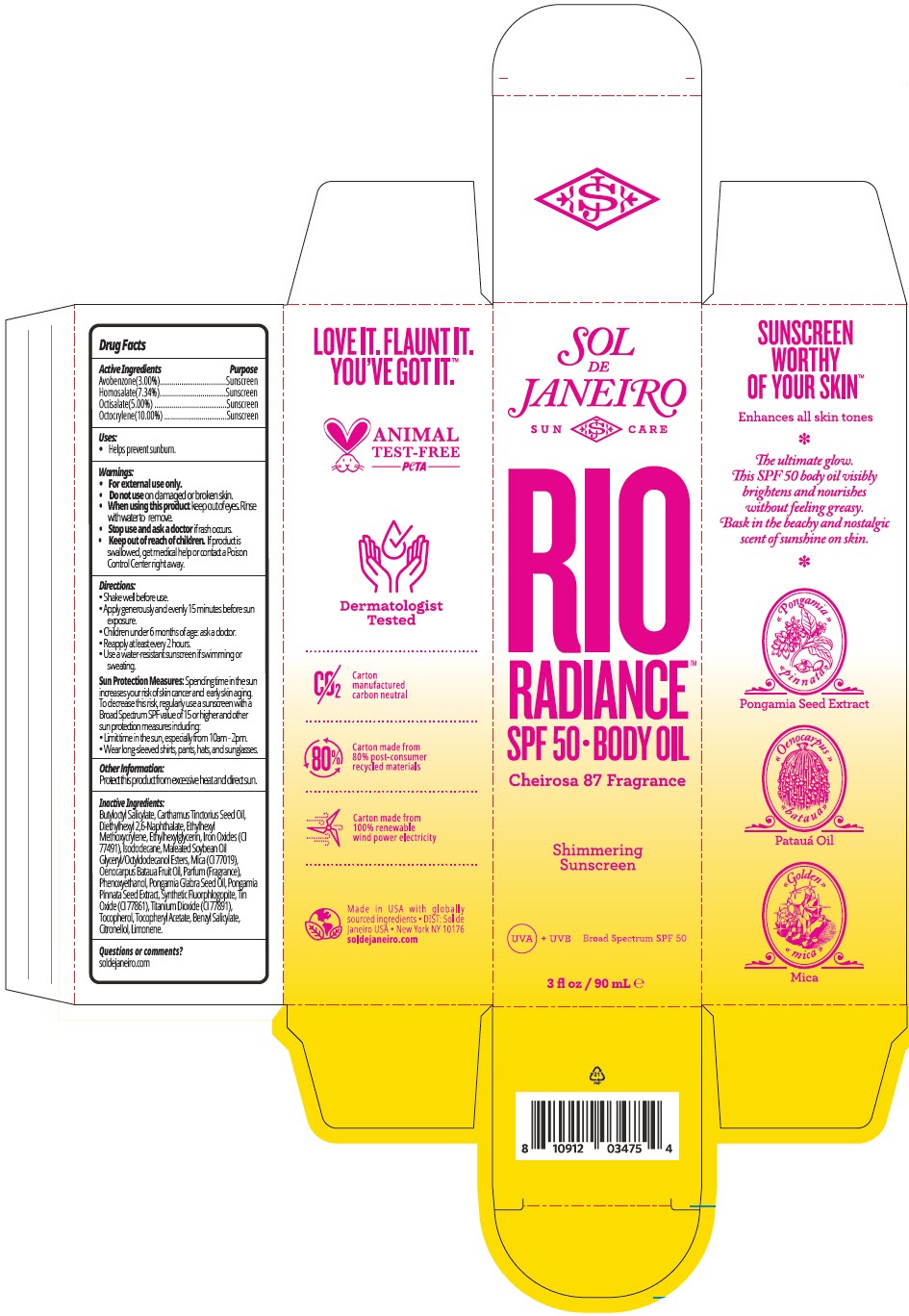 DRUG LABEL: Sol de Janiero Rio Radiance SPF 50 Body
NDC: 66163-4837 | Form: OIL
Manufacturer: Cosmetic Solutions LLC
Category: otc | Type: HUMAN OTC DRUG LABEL
Date: 20240318

ACTIVE INGREDIENTS: Avobenzone 30 mg/1 mL; Homosalate 77.4 mg/1 mL; Octisalate 50 mg/1 mL; Octocrylene 100 mg/1 mL
INACTIVE INGREDIENTS: BUTYLOCTYL SALICYLATE; SAFFLOWER OIL; DIETHYLHEXYL 2,6-NAPHTHALATE; ETHYLHEXYL METHOXYCRYLENE; ETHYLHEXYLGLYCERIN; FERRIC OXIDE RED; ISODODECANE; MICA; OENOCARPUS BATAUA FRUIT OIL; PHENOXYETHANOL; KARUM SEED OIL; PONGAMIA PINNATA SEED; STANNIC OXIDE; TITANIUM DIOXIDE; TOCOPHEROL; .ALPHA.-TOCOPHEROL ACETATE; BENZYL SALICYLATE; .BETA.-CITRONELLOL, (R)-; LIMONENE, (+)-

Sol de Janiero Rio Radiance™ SPF 50 Body Oil

Drug Facts

ACTIVE INGREDIENT

Active Ingredients | Purpose
Avobenzone(3.00%) | Sunscreen
Homosalate(7.34%) | Sunscreen
Octisalate(5.00%) | Sunscreen
Octocrylene(10.00%) | Sunscreen

Uses

- Helps prevent sunburn.

Warnings

- For external use only.

- Do not use on damaged or broken skin.

- When using this product keep out of eyes. Rinse with water to remove.

- Stop use and ask a doctor if rash occurs.

- Keep out of reach of children. If product is swallowed, get medical help or contact a Poison Control Center right away.

Directions

- Shake well before use.
- Apply generously and evenly 15 minutes before sun exposure.
- Children under 6 months of age: ask a doctor.
- Reapply at least every 2 hours.
- Use a water-resistant sunscreen if swimming or sweating.

Sun Protection Measures: Spending time in the sun increases your risk of skin cancer and early skin aging. To decrease this risk, regularly use a sunscreen with a Broad Spectrum SPF value of 15 or higher and other sun protection measures including:

- Limit time in the sun, especially from 10am - 2pm.
- Wear long-sleeved shirts, pants, hats, and sunglasses.

Other Information

Protect this product from excessive heat and direct sun.

Inactive Ingredients

Butyloctyl Salicylate, Carthamus Tinctorius Seed Oil, Diethylhexyl 2,6-Naphthalate, Ethylhexyl Methoxycrylene, Ethylhexylglycerin, Iron Oxides (CI 77491), Isododecane, Maleated Soybean Oil Glyceryl/Octyldodecanol Esters, Mica (CI 77019), Oenocarpus Bataua Fruit Oil, Parfum (Fragrance), Phenoxyethanol, Pongamia Glabra Seed Oil, Pongamia Pinnata Seed Extract, Synthetic Fluorphlogopite, Tin Oxide (CI 77861), Titanium Dioxide (CI 77891), Tocopherol, Tocopheryl Acetate, Benzyl Salicylate, Citronellol, Limonene.

Questions or comments?

soldejaneiro.com

PRINCIPAL DISPLAY PANEL - 90 mL Cylinder Carton

SOL
DE
JANEIRO

SUN CARE

RIO
RADIANCE™

SPF 50 • BODY OIL

Cheirosa 87 Fragrance

Shimmering
Sunscreen

UVA + UVB

Broad Spectrum SPF 50

3 fl oz / 90 mL ℮